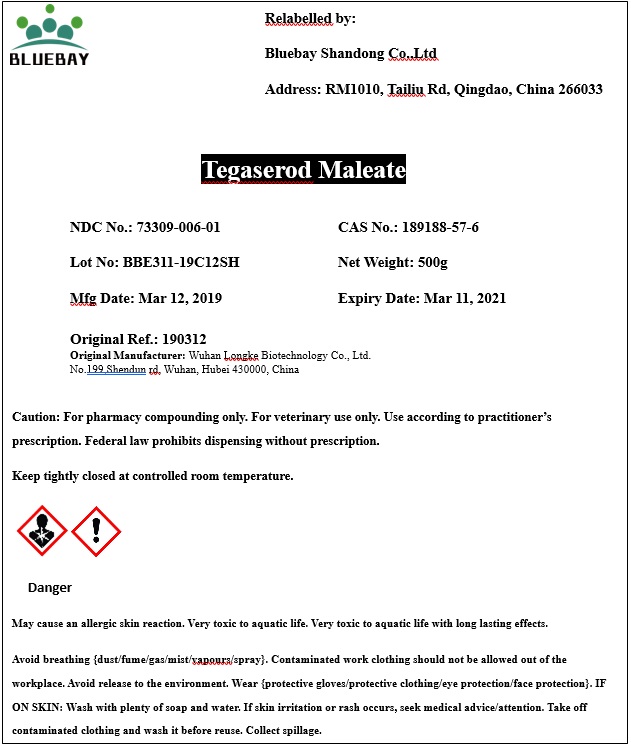 DRUG LABEL: Tegaserod Maleate
NDC: 73309-006 | Form: POWDER
Manufacturer: BLUEBAY SHANDONG CO.,LTD
Category: other | Type: BULK INGREDIENT
Date: 20190820

ACTIVE INGREDIENTS: TEGASEROD MALEATE 1 g/1 g

Tegaserod Maleate